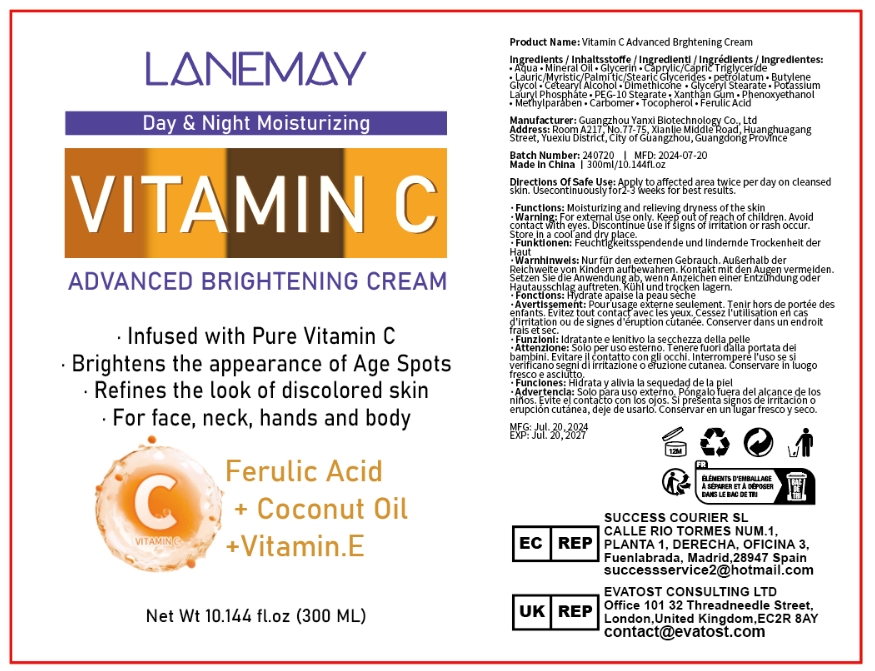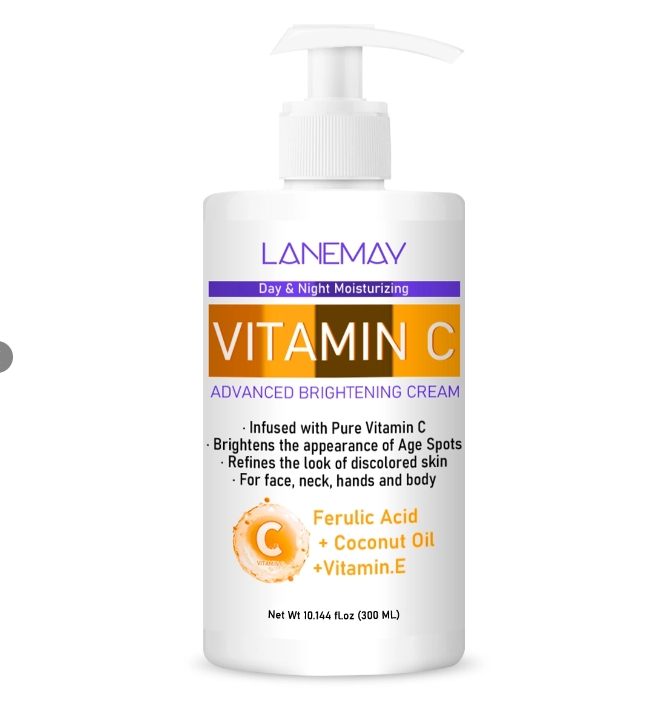 DRUG LABEL: Vitamin C Advanced Brightening Cream
NDC: 84025-127 | Form: CREAM
Manufacturer: Guangzhou Yanxi Biotechnology Co., Ltd
Category: otc | Type: HUMAN OTC DRUG LABEL
Date: 20240812

ACTIVE INGREDIENTS: MINERAL OIL 5 mg/100 mL; GLYCERIN 3 mg/100 mL
INACTIVE INGREDIENTS: WATER

DOSAGE AND ADMINISTRATION

For face,neck, hands and body

WARNINGS

keep out of children

INACTIVE INGREDIENT

Aqua

INDICATIONS AND USAGE

For face,neck, hands and body care

keep out of children

PURPOSE

1.Brightens the appearance of Age Spots.

2.Refines the look of discolored skin.